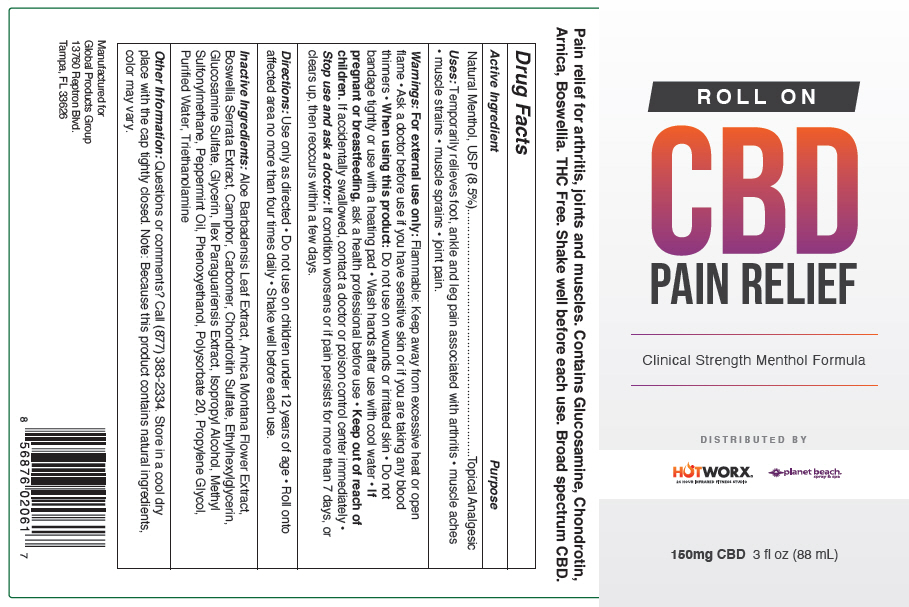 DRUG LABEL: CBD Pain Relief 
NDC: 72593-157 | Form: GEL
Manufacturer: Global Products Group, LLC
Category: otc | Type: HUMAN OTC DRUG LABEL
Date: 20220125

ACTIVE INGREDIENTS: MENTHOL, UNSPECIFIED FORM 85 mg/1 mL
INACTIVE INGREDIENTS: ALOE VERA LEAF; ARNICA MONTANA WHOLE; INDIAN FRANKINCENSE; CAMPHOR (SYNTHETIC); CANNABIS SATIVA SEED OIL; CARBOMER INTERPOLYMER TYPE A (ALLYL SUCROSE CROSSLINKED); CHONDROITIN SULFATE (SHARK); GLUCOSAMINE SULFATE POTASSIUM CHLORIDE; GLYCERIN; ILEX PARAGUARIENSIS LEAF; ISOPROPYL ALCOHOL; ETHYLHEXYLGLYCERIN; PHENOXYETHANOL; DIMETHYL SULFONE; PEPPERMINT OIL; POLYSORBATE 20; PROPYLENE GLYCOL; TROLAMINE; WATER

CBD Pain Relief
Clinical Strength Menthol Formula

Drug Facts

Active Ingredient

Natural Menthol, USP (8.5%)

Purpose

Topical Analgesic

Uses

Temporarily relieves foot, ankle and leg pain associated with arthritis

- muscle aches
- muscle strains
- muscle sprains
- joint pain.

Warnings

For external use only: Flammable: Keep away from excessive heat or open flame

- Ask a doctor before use if you have sensitive skin or if you are taking any blood thinners

- When using this product: Do not use on wounds or irritated skin
- Do not bandage tightly or use with a heating pad
- Wash hands after use with cool water

PREGNANCY OR BREAST FEEDING

- If pregnant or breastfeeding, ask a health professional before use

- Keep out of reach of children. If accidentally swallowed, contact a doctor or poison control center immediately

- Stop use and ask a doctor: If condition worsens or if pain persists for more than 7 days, or clears up, then reoccurs within a few days.

Directions

Use only as directed

- Do not use on children under 12 years of age
- Roll onto affected area no more than four times daily
- Shake well before each use.

Inactive Ingredients

Aloe Barbadensis Leaf Extract, Arnica Montana Flower Extract, Boswellia Serrata Extract, Camphor, Carbomer, Chondroitin Sulfate, Ethylhexylglycerin, Glucosamine Sulfate, Glycerin, Ilex Paraguariensis Extract, Isopropyl Alcohol, Methyl Sulfonylmethane, Peppermint Oil, Phenoxyethanol, Polysorbate 20, Propylene Glycol, Purified Water, Triethanolamine

Other Information

Questions or comments?

Call (877) 383-2334. Store in a cool dry place with the cap tightly closed. Note: Because this product contains natural ingredients, color may vary.

DISTRIBUTED BY

HOTWORX®
24 HOUR INFRARED FITNESS STUDIO

planet beach®
spray & spa

PRINCIPAL DISPLAY PANEL - 88 mL Bottle Label

ROLL ON

CBD
PAIN RELIEF

Clinical Strength Menthol Formula

DISTRIBUTED BY

HOTWORX®
24 HOUR INFRARED FITNESS STUDIO

planet beach®
spray & spa

150mg CBD 3 fl oz (88 mL)